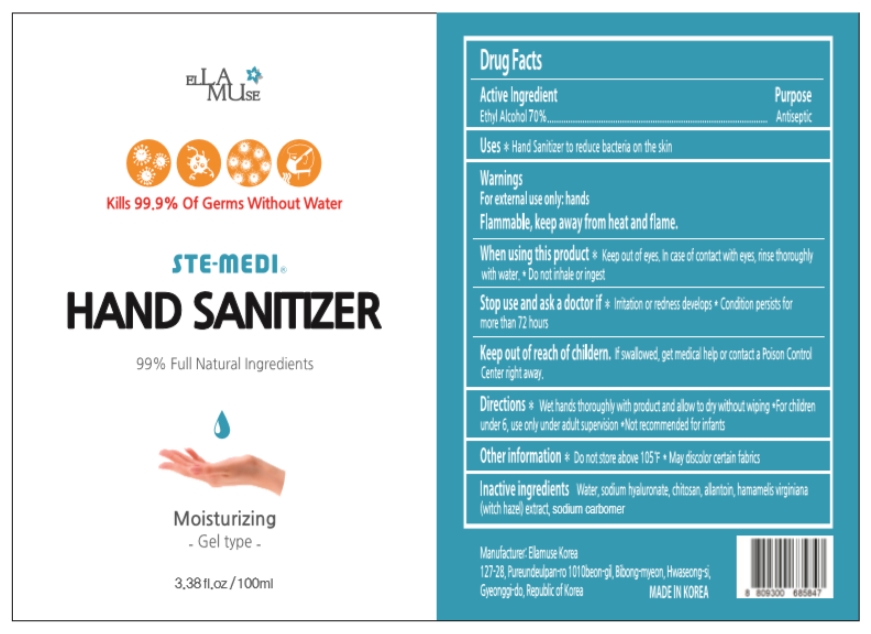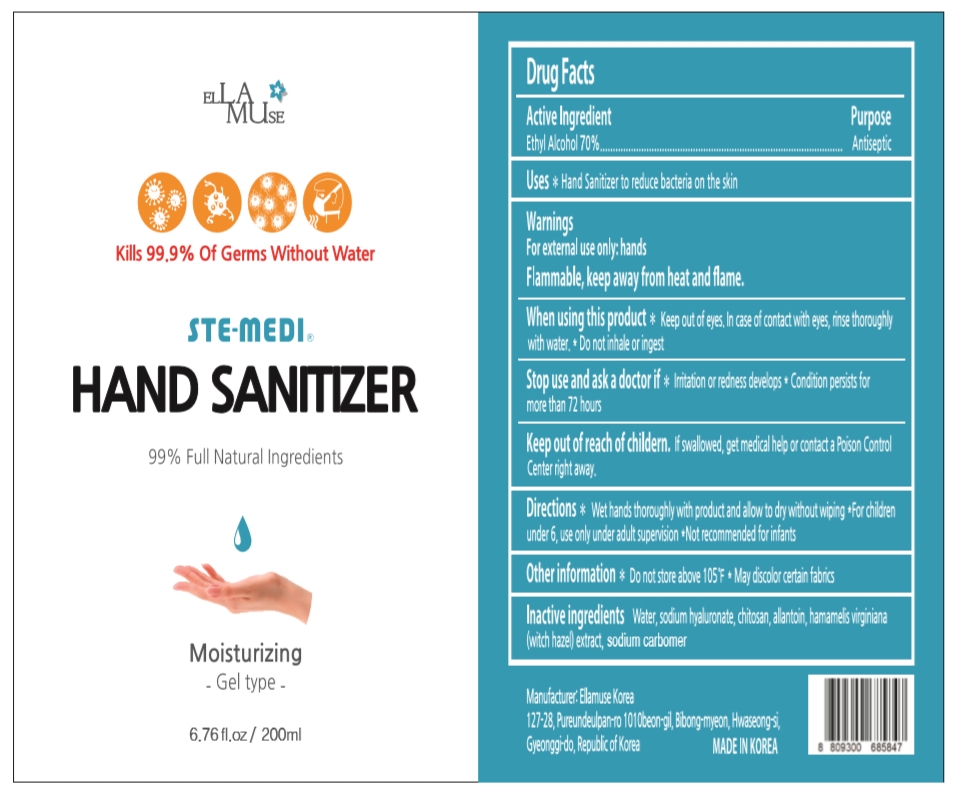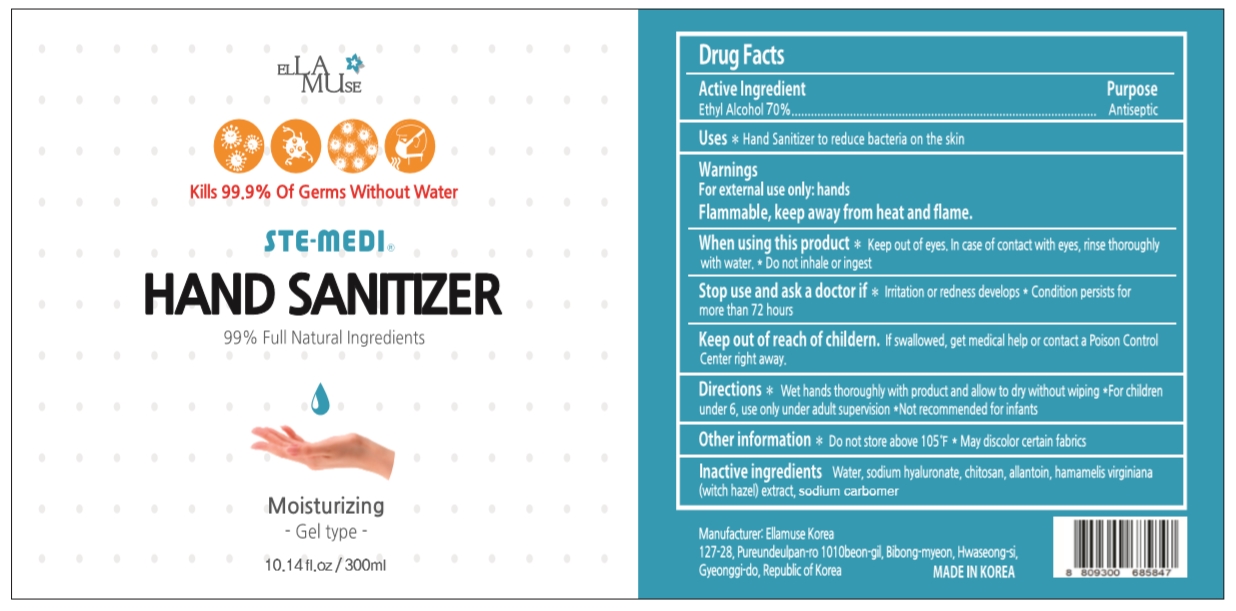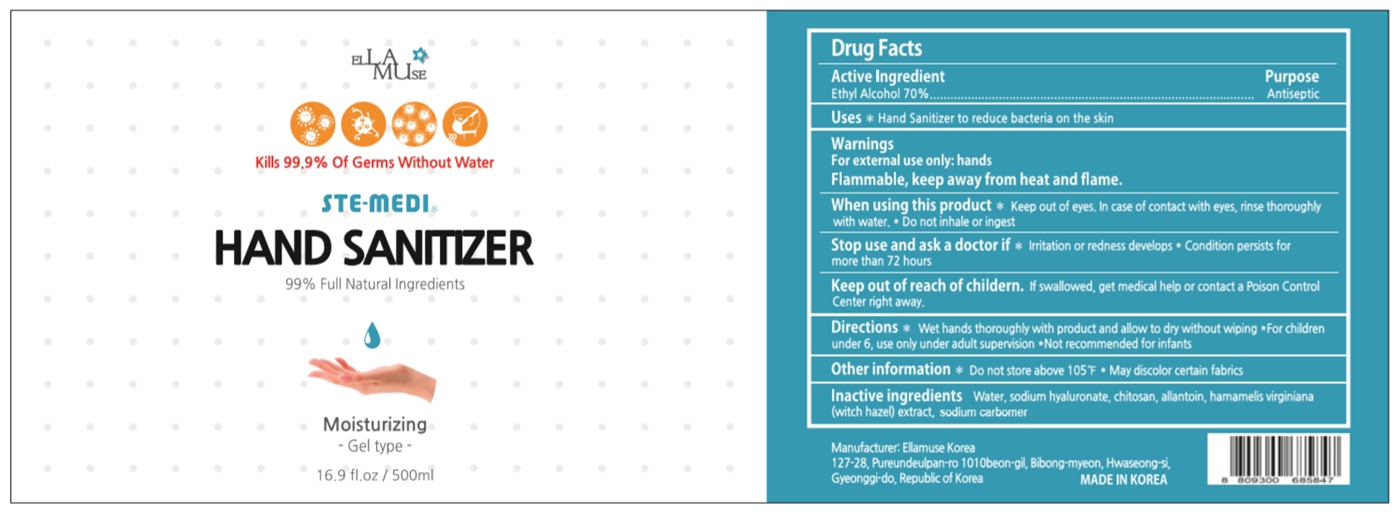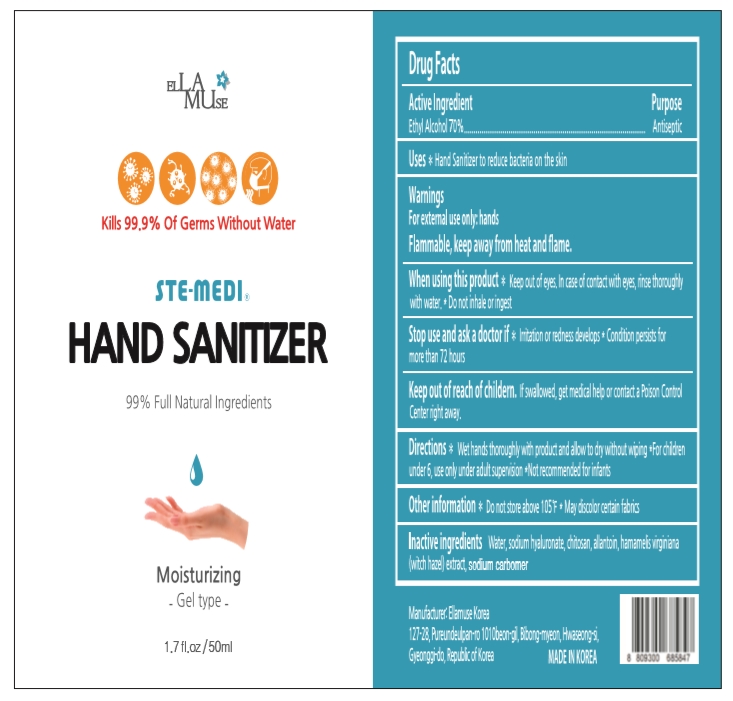 DRUG LABEL: STE-MEDI
NDC: 77599-201 | Form: GEL
Manufacturer: ELLAMUSE KOREA
Category: otc | Type: HUMAN OTC DRUG LABEL
Date: 20200509

ACTIVE INGREDIENTS: ALCOHOL 70 mL/100 mL
INACTIVE INGREDIENTS: ALLANTOIN; HYALURONATE SODIUM; WATER; POLIGLUSAM HYDROCHLORIDE; HAMAMELIS VIRGINIANA TOP; CARBOMER HOMOPOLYMER, UNSPECIFIED TYPE

Active Ingredient

Ethyl Alcohol 70%

Purpose

Antiseptic

Uses

Hand Sanitizer to reduce bacteria on the skin

Warnings

For external use only: hands

Flammable, keep away from heat and flame.

When using this product

Keep out of eyes. In case of contact with eyes, nise thoroughly with water. Do not inhale or ingest.

Stop use and ask a doctor if

Irritation or redness develops. Condition persists for more than 72 hours.

Keep out of reach of children.

If swallowed, get medical help or contact a Poison Control Center right away.

Directions

Wet hands thoroughly with product and allow to dry without wiping. For children under 6, use only under adult supervision. Not recommended for infants.

Other information

Do not store above 105F. May discolor certain fabrics.

Inactive ingredients

Water, Sodium Hyaluronate, Chitosan, Allantoin, Hamamelis Virginiana (Witch Hazel) Extract, Carbomer